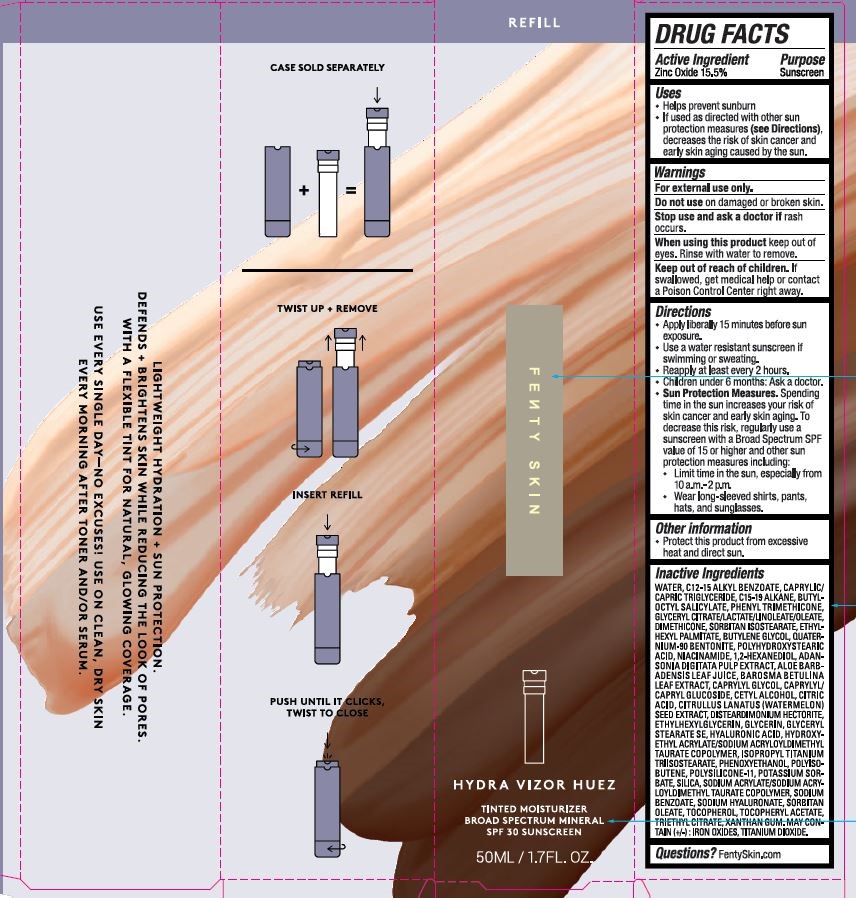 DRUG LABEL: HYDRA VIZOR HUEZ TINTED MOISTURIZER
NDC: 71499-083 | Form: LOTION
Manufacturer: KENDO HOLDINGS INC.
Category: otc | Type: HUMAN OTC DRUG LABEL
Date: 20260116

ACTIVE INGREDIENTS: ZINC OXIDE 15.5 g/100 mL
INACTIVE INGREDIENTS: BUTYLENE GLYCOL; ISOPROPYL TITANIUM TRIISOSTEARATE; SODIUM ACRYLATE/SODIUM ACRYLOYLDIMETHYLTAURATE COPOLYMER (4000000 MW); SODIUM BENZOATE; HYALURONATE SODIUM; CAPRYLYL/CAPRYL OLIGOGLUCOSIDE; SORBITAN ISOSTEARATE; ANHYDROUS CITRIC ACID; CETYL ALCOHOL; WATERMELON SEED; DISTEARDIMONIUM HECTORITE; GLYCERYL STEARATE SE; .ALPHA.-TOCOPHEROL; PHENYL TRIMETHICONE; GLYCERYL CITRATE/LACTATE/LINOLEATE/OLEATE; HYALURONIC ACID; DIMETHICONE/VINYL DIMETHICONE CROSSPOLYMER (SOFT PARTICLE); POTASSIUM SORBATE; XANTHAN GUM; PHENOXYETHANOL; SILICON DIOXIDE; C15-19 ALKANE; BUTYLOCTYL SALICYLATE; .ALPHA.-TOCOPHEROL ACETATE; TRIETHYL CITRATE; ETHYLHEXYL PALMITATE; QUATERNIUM-90 BENTONITE; NIACINAMIDE; ADANSONIA DIGITATA FRUIT PULP; BROWN IRON OXIDE; POLYHYDROXYSTEARIC ACID (2300 MW); POLYISOBUTYLENE (1300 MW); TITANIUM DIOXIDE; GLYCERIN; HYDROXYETHYL ACRYLATE/SODIUM ACRYLOYLDIMETHYL TAURATE COPOLYMER (45000 MPA.S AT 1%); SORBITAN MONOOLEATE; AGATHOSMA BETULINA LEAF; MEDIUM-CHAIN TRIGLYCERIDES; 1,2-HEXANEDIOL; CAPRYLYL GLYCOL; ALKYL (C12-15) BENZOATE; DIMETHICONE 20; ALOE VERA LEAF; WATER; ETHYLHEXYLGLYCERIN

KENDO - HYDRA VIZOR HUEZ TINTED MOISTURIZER BROAD SPECTRUM SPF 30

ACTIVE INGREDIENT

ZINC OXIDE 15.5%

PURPOSE

SUNSCREEN

USES

HELPS PREVENT SUNBURN
IF USED AS DIRECTED WITH OTHER SUN PROTECTION MEASURES (SEE DIRECTIONS), DECREASES THE RISK OF SKIN CANCER AND EARLY SKIN AGING CAUSED BY THE SUN.

WARNINGS

FOR EXTERNAL USE ONLY.

DO NOT USE ON DAMAGED OR BROKEN SKIN.

STOP USE AND ASK A DOCTOR IF RASH OCCURS.

WHEN USING THIS PRODUCT KEEP OUT OF EYES. RINSE WITH WATER TO REMOVE.

KEEP OUT OF REACH OF CHILDREN. IF SWALLOWED, GET MEDICAL HELP OR CONTACT A POISON CONTROL CENTER RIGHT AWAY.

KEEP OUT OF REACH OF CHILDREN. IF SWALLOWED, GET MEDICAL HELP OR CONTACT A POISON CONTROL CENTER RIGHT AWAY.

DIRECTIONS

APPLY LIBERALLY 15 MINUTES BEFORE SUN EXPOSURE.
USE A WATER RESISTANT SUNSCREEN IF SWIMMING OR SWEATING.
REAPPLY AT LEAST EVERY 2 HOURS.
CHILDREN UNDER 6 MONTHS: ASK A DOCTOR.
SUN PROTECTION MEASURES. SPENDING TIME IN THE SUN INCREASES YOUR RISK OF SKIN CANCER AND EARLY SKIN AGING. TO DECREASE THIS RISK, REGULARLY USE A SUNCREEN WITH A BROAD SPECTRUM SPF VALUE OF 15 OR HIGHER AND OTHER SUN PROTECTION MEASURES INCLUDING:
LIMIT TIME IN THE SUN, ESPECIALLY FROM 10 A.M. - 2 P.M.
WEAR LONG=SLEEVED SHIRTS, PANTS, HATS, AND SUNGLASSES.

OTHER INFORMATION

PROTECT THIS PRODUCT FROM EXCESSIVE HEAT AND DIRECT SUN.

INACTIVE INGREDIENTS

WATER, C12-15 ALKYL BENZOATE, CAPRYLIC/CAPRIC TRIGLYCERIDE, C15-19 ALKANE, BUTYLOCTYL SALICYLATE, PHENYL TRIMETHICONE, GLYCERYL CITRATE/LACTATE/LINOLEATE/OLEATE, DIMETHICONE, SORBITAN ISOSTEARATE, ETHYLHEXYL PALMITATE, BUTYLENE GLYCOL, QUATERNIUM-90 BENTONITE, POLYHYDROXYSTEARIC ACID, NIACINAMIDE, 1,2-HEXANEDIOL, ADANSONIA DIGITATA PULP EXTRACT, ALOE BARBADENSIS LEAF JUICE, BAROSMA BETULINA LEAF EXTRACT, CAPRYLYL GLYCOL, CAPRYLYL/CAPRYL GLUCOSIDE, CETYL ALCOHOL, CITRIC ACID, CITRULLUS LANATUS (WATERMELON) SEED EXTRACT, DISTEARDIMONIUM HECTORITE, ETHYLHEXYLGLYCERIN, GLYCERIN, GLYCERYL STEARATE SE, HYALURONIC ACID, HYDROXYETHYL ACRYLATE/SODIUM ACRYLOYLDIMETHYL TAURATE COPOLYMER, ISOPROPYL TITANIUM TRIISOSTEARATE, PHENOXYETHANOL, POLYISOBUTENE, POLYSILICONE-11, POTASSIUM SORBATE, SILICA, SODIUM ACRYLATE/SODIUM ACRYLOYLDIMETHYL TAURATE COPOLYMER, SODIUM BENZOATE, SODIUM HYALURONATE, SORBITAN OLEATE, TOCOPHEROL, TOCOPHERYL ACETATE, TRIETHYL CITRATE, XANTHAN GUM. MAY CONTAIN (+/-): IRON OXIDES,TITANIUM DIOXIDE.

QUESTIONS?

FENTYSKIN.COM